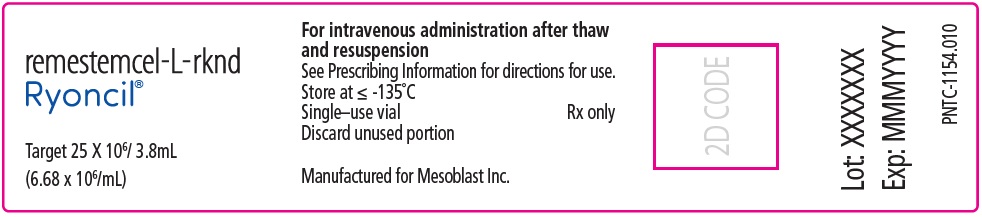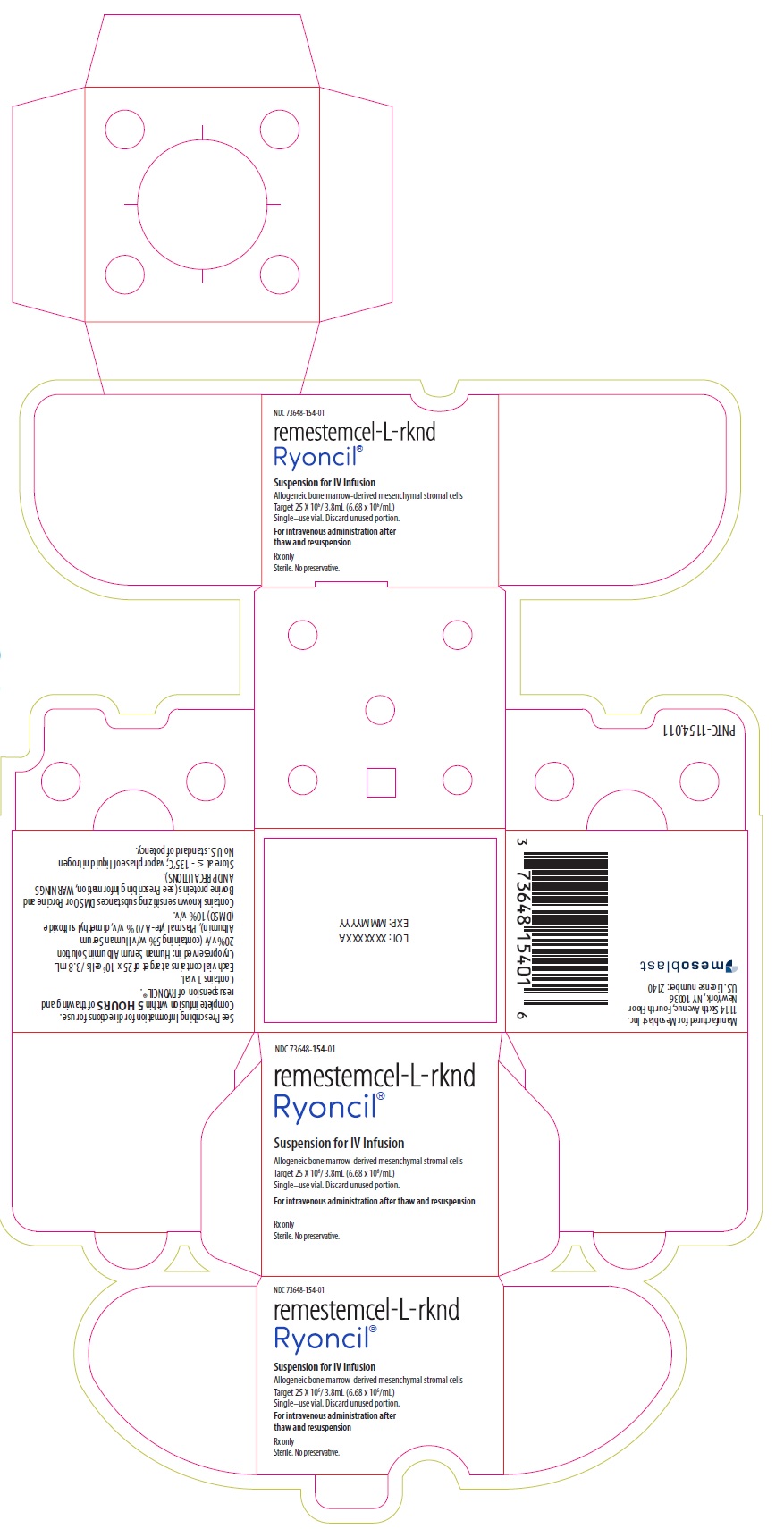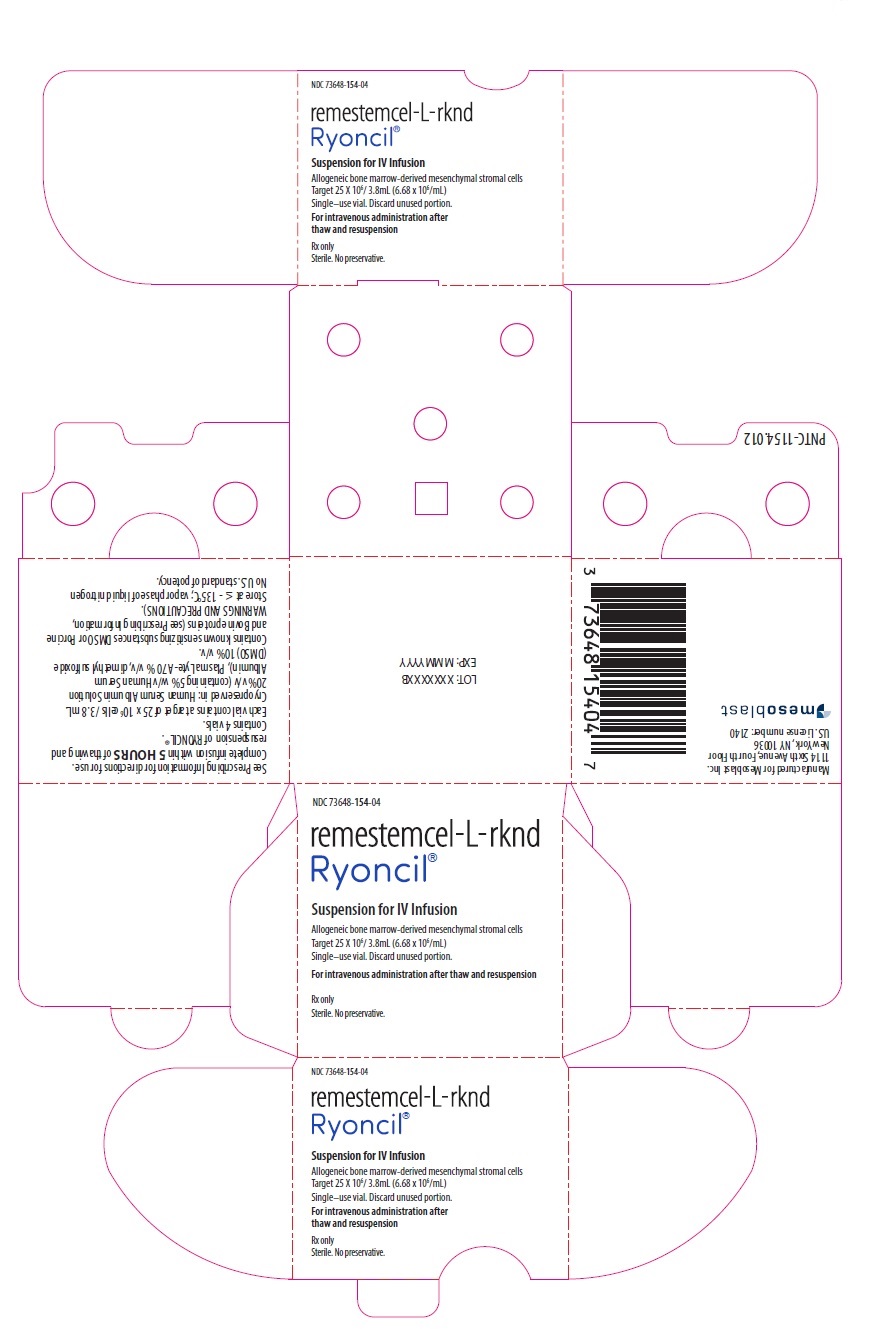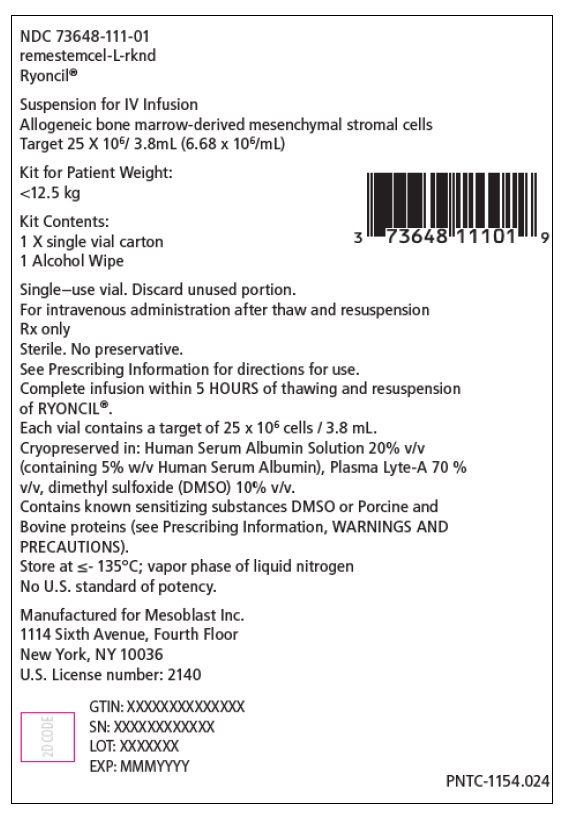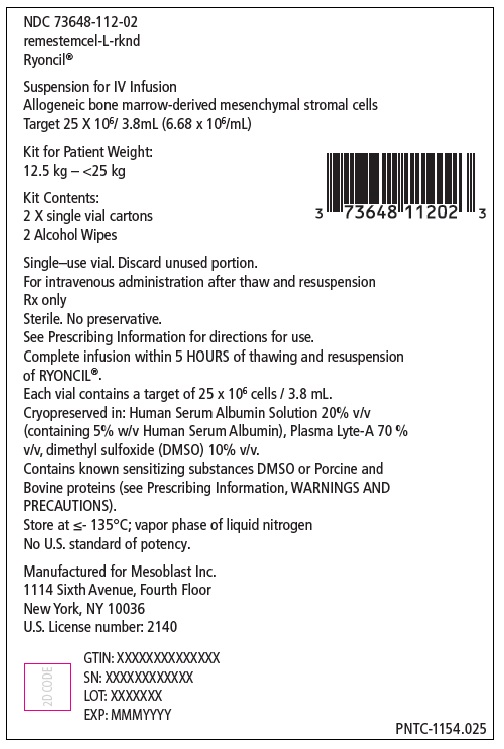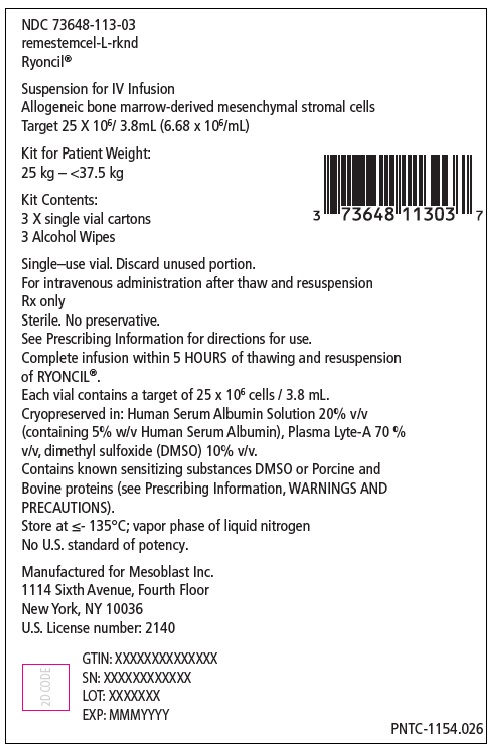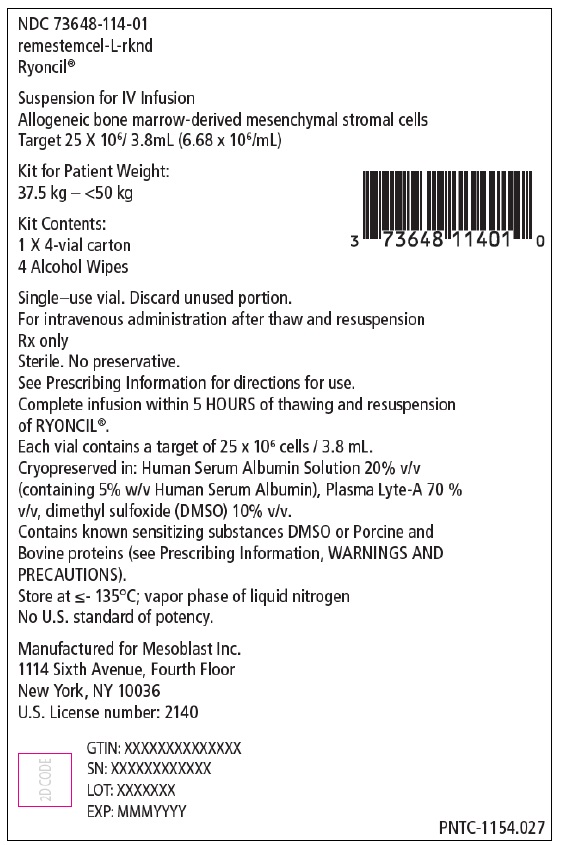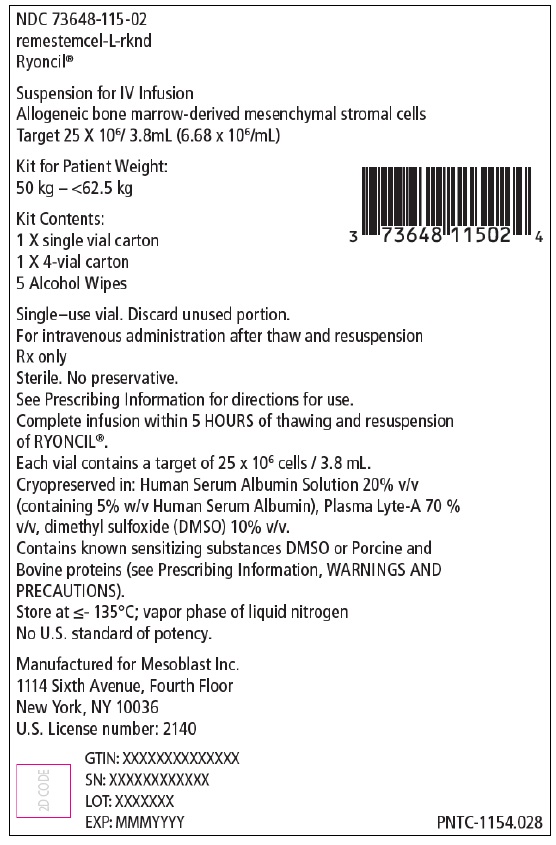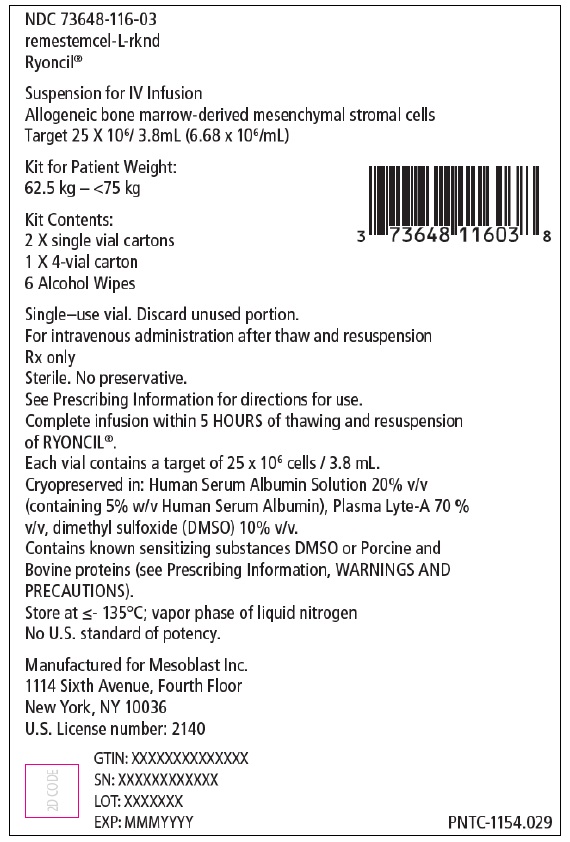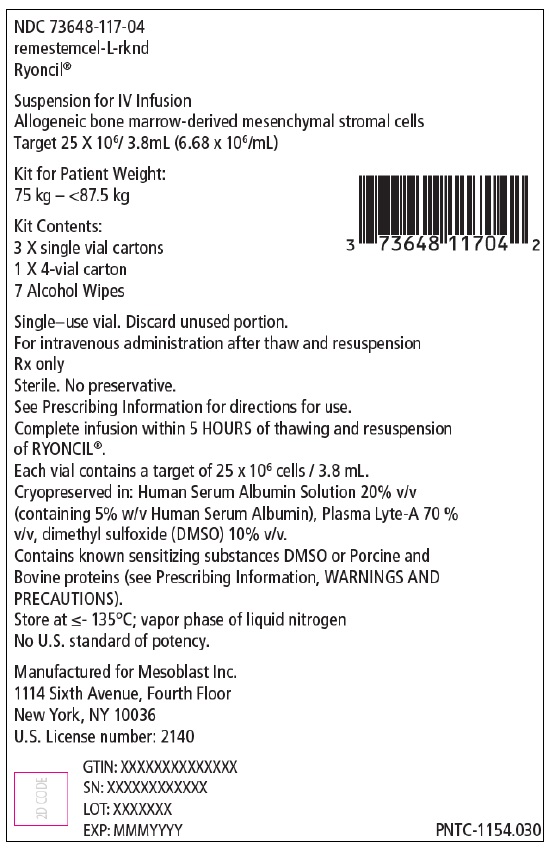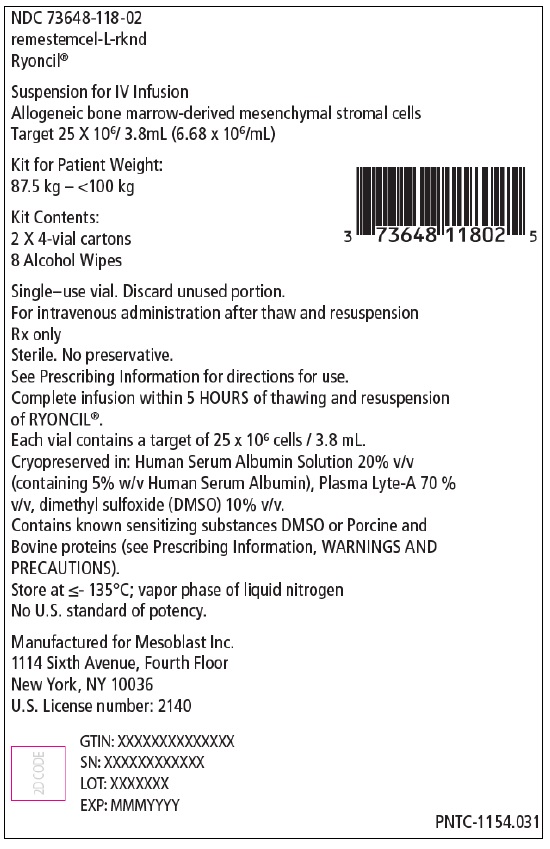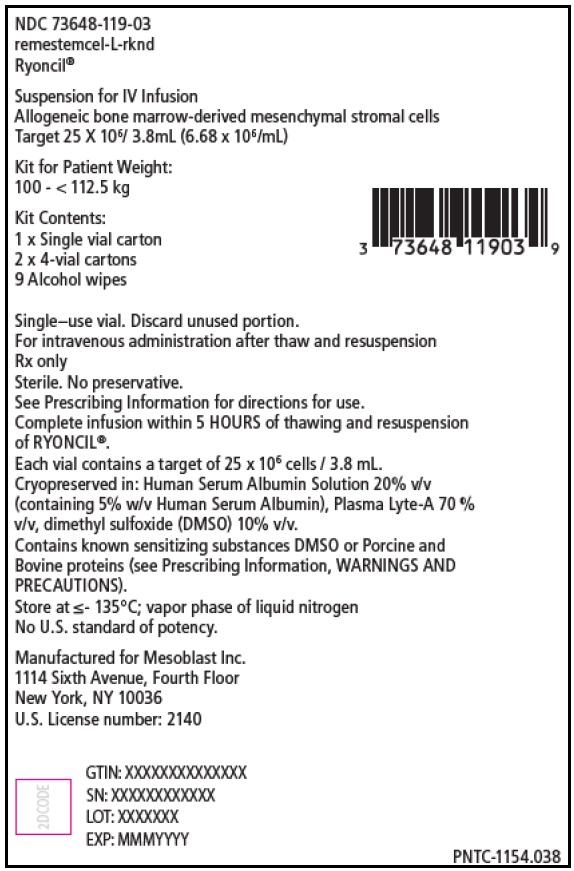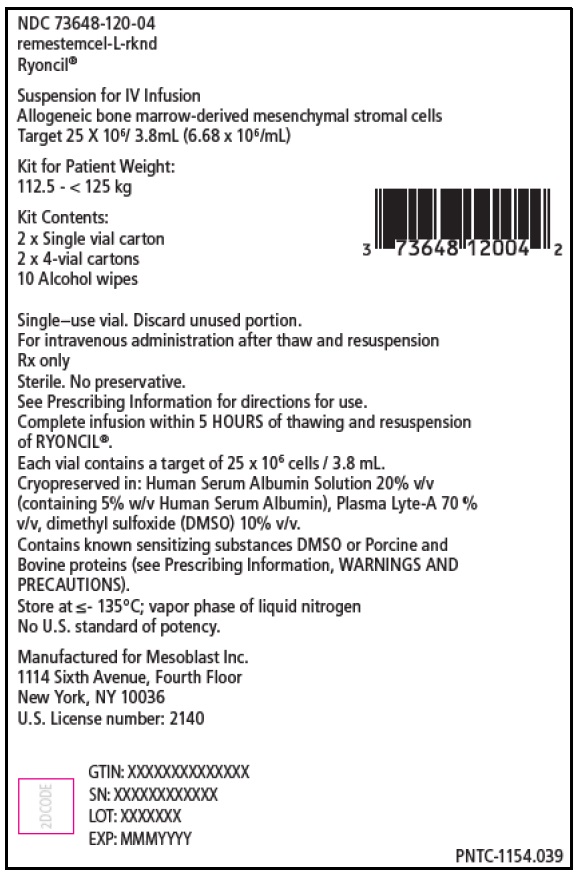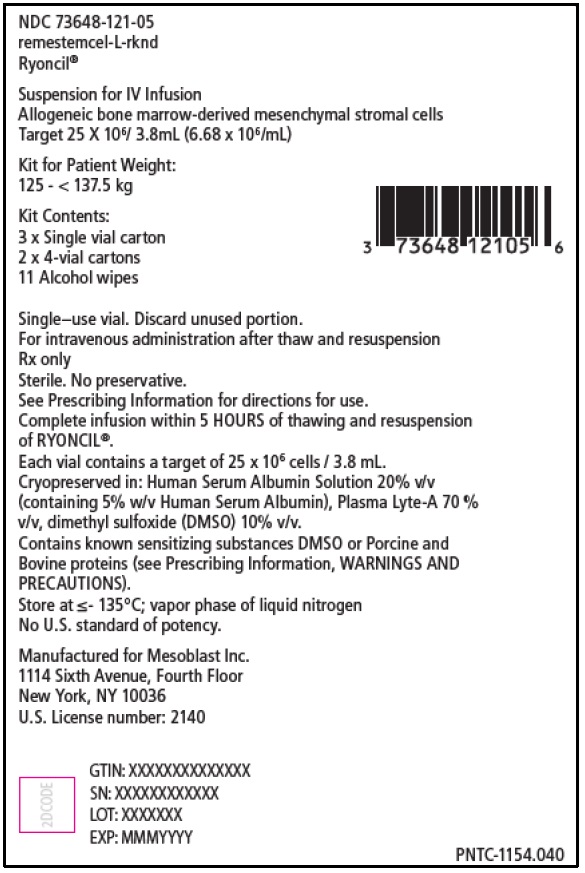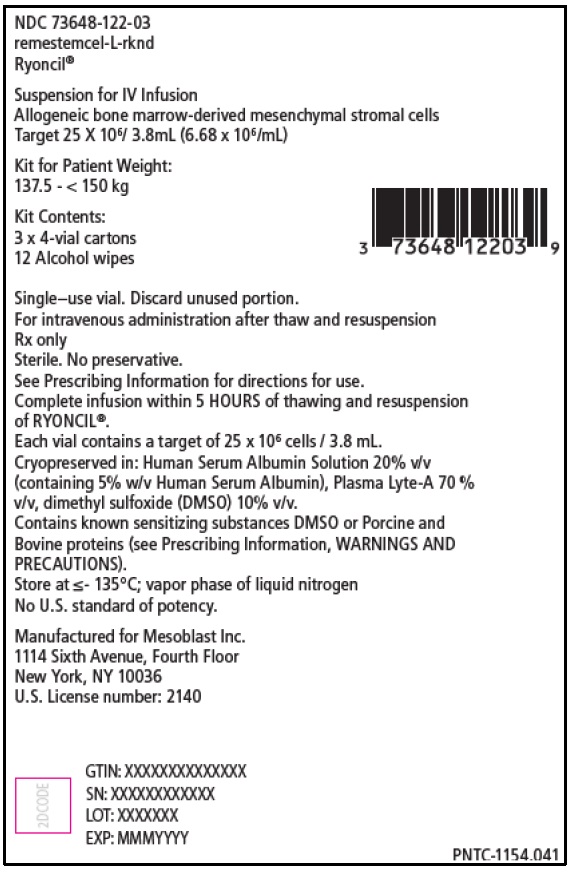 DRUG LABEL: RYONCIL
NDC: 73648-111 | Form: KIT | Route: INTRAVENOUS
Manufacturer: Mesoblast
Category: prescription | Type: HUMAN PRESCRIPTION DRUG LABEL
Date: 20250911

ACTIVE INGREDIENTS: ALLOGENIC BONE-MARROW-DERIVED MESENCHYMAL STEM CELLS 6680000 [arb'U]/1 mL; ISOPROPYL ALCOHOL 0.7 mL/1 mL
INACTIVE INGREDIENTS: PLASMALYTE A; DIMETHYL SULFOXIDE; ALBUMIN HUMAN; WATER

HIGHLIGHTS OF PRESCRIBING INFORMATION

These highlights do not include all the information needed to use RYONCIL® safely and effectively. See full prescribing information for RYONCIL®.
RYONCIL® (remestemcel-L-rknd) suspension for intravenous infusion
Initial U.S. Approval: December 2024

RECENT MAJOR CHANGES

How Supplied/Storage and Handling (16) | 09/2025

1 INDICATIONS AND USAGE

RYONCIL is an allogeneic bone marrow-derived mesenchymal stromal cell (MSC) therapy indicated for the treatment of steroid-refractory acute graft versus host disease (SR-aGvHD) in pediatric patients 2 months of age and older.

2 DOSAGE AND ADMINISTRATION

For intravenous use only.

- The recommended dosage of RYONCIL is 2 × 10^6 MSC/kg body weight per intravenous infusion given twice per week for 4 consecutive weeks. Infusions should be administered at least 3 days apart.
- Assess response 28 ± 2 days after the first dose and administer further treatment as appropriate as described in the table below.

Recommended Treatment Based on Day 28 Response
Response | Recommendation
Complete Response (CR) | No further treatment with RYONCIL
Partial or Mixed Response | Repeat administration of RYONCIL once a week for additional 4 weeks (4 infusions total)
No Response | Consider alternative treatments
Recurrence of GvHD after CR | Repeat administration of RYONCIL twice a week for an additional 4 consecutive weeks (8 infusions total)

3 DOSAGE FORMS AND STRENGTHS

RYONCIL is available as a cell suspension for intravenous infusion in a target concentration of 6.68 X 10^6 MSCs per mL in 3.8 mL contained in a 6 mL cryovial.

4 CONTRAINDICATIONS

Known hypersensitivity to dimethyl sulfoxide (DMSO) or Porcine and Bovine proteins. (4)

5 WARNINGS AND PRECAUTIONS

Hypersensitivity/Acute Infusion reactions: Monitor for hypersensitivity reactions during infusion and premedicate with corticosteroids and antihistamines. (5.1)

Transmission of Infectious Agents: RYONCIL may transmit infectious agents. (5.2)

Ectopic Tissue Formation: Ectopic tissue formation may occur following treatment with RYONCIL. (5.3)

6 ADVERSE REACTIONS

The most common non-laboratory adverse reactions (incidence ≥20%) are: viral infectious disorders, bacterial infectious disorders, infection – pathogen unspecified, pyrexia, hemorrhage, edema, abdominal pain and hypertension (6.1).

To report SUSPECTED ADVERSE REACTIONS, contact Mesoblast at toll-free phone #1-844-889-MESO (6376) or FDA at 1-800-FDA-1088 or www.fda.gov/medwatch.

FULL PRESCRIBING INFORMATION

1 INDICATIONS AND USAGE

RYONCIL is indicated for the treatment of steroid refractory acute graft versus host disease (SR-aGvHD) in pediatric patients 2 months of age and older.

2 DOSAGE AND ADMINISTRATION

For intravenous use only.

2.1 Recommended Dosage

- The recommended dosage of RYONCIL is 2 × 10^6 mesenchymal stromal cells (MSC)/kg body weight per intravenous infusion given twice a week for 4 consecutive weeks for a total of 8 infusions. Administer infusions at least 3 days apart.
- Assess response 28 ± 2 days after the first dose and administer further treatment as appropriate as described in Table 1 based on Day 28 response.

Table 1: Recommended Treatment based on Day 28 Response
Response | Recommendation
Complete Response | No further treatment with RYONCIL
Partial or Mixed Response [Partial response defined as organ improvement of at least one stage without worsening in any other organ, whereas mixed response was defined as improvement of at least one evaluable organ with worsening in another organ as per International Blood and Marrow Transplantation Registry Severity Index Criteria grading system.] | Repeat administration of RYONCIL once a week for additional 4 weeks (4 infusions total)
No Response | Consider alternative treatments
Recurrence of GvHD after complete response | Repeat administration of RYONCIL twice a week for an additional 4 consecutive weeks (8 infusions total)

2.2 Preparation and Administration Instructions

Receipt and Storage of RYONCIL

RYONCIL is shipped directly to the clinical facility in a liquid nitrogen dry shipper maintained at a temperature of ≤ -135°C.

RYONCIL must remain frozen at ≤ -135°C in liquid nitrogen vapor phase until thawed immediately prior to administration [see How Supplied/Storage and Handling (16)].

Preparation

RYONCIL and Plasma-Lyte® A should be prepared following aseptic technique in a Biological Safety Cabinet (BSC). Spray and wipe down the following materials with 70% alcohol prior to transferring them into the BSC preparation area. All materials should remain in the BSC preparation area unless discarded.

Prepare a sterile water bath to a minimum depth of 4 inches and warm to 37°C (± 2°C) at least 30 minutes prior for thawing.

Supplies needed for preparation of RYONCIL and Plasma-Lyte® A

- RYONCIL vials
- Plasma-Lyte® A
- Infusion bag
- Interlink blood bag spikes (2)
- Interlink threaded lock cannula (1 per syringe)
- 60 mL luer-lock syringe (1)
- 5 mL luer-lock syringe (1 per each thawed vial)
- 18-gauge needle (1 per each thawed vial)
  Note: Use a 1mL syringe if volume to be removed from vial is less than 1mL
- Airtight zip seal plastic bag(s) (1 per each vial for thaw)
- Water bath
- Alcohol wipes

Note: Plasma-Lyte® A may be substituted by Plasma-Lyte® 148 (pH 7.4 with no glucose).

Preparation of Plasma-Lyte® A

1- Insert the Interlink blood bag spike into the Plasma-Lyte® A bag.
2- Aseptically attach the threaded lock cannula to a 60 mL syringe.
3- Use an alcohol wipe to scrub the membrane of the Plasma-Lyte® A bag interlink spike injection site.
4- Attach the threaded lock cannula/syringe assembly to the Plasma-Lyte® A bag to the injection site.
5- Measure and withdraw 40 mL of Plasma-Lyte® A from the bag

Note: DO NOT remove the syringe containing Plasma-Lyte® A from the Plasma-Lyte® A bag. Set aside for later use.

Preparation of RYONCIL

1. Prior to RYONCIL thaw, verify that the pre-arranged time for the RYONCIL administration is still feasible. Patient infusion must occur within 5 hours from the start time of first vials of RYONCIL thaw.
2. Remove RYONCIL vial(s) from cryo-storage.
3. Place vial(s) into an airtight zip seal plastic bag(s) and immerse closed bag(s) into the water bath (37ºC), maintaining the top closure above the water line. Use a separate zip seal plastic bag for each vial of RYONCIL.
  Note: A maximum of 4 vials can be thawed in the water bath at the same time.
4. To thaw, gently agitate the sealed zip seal bag(s) with the vial(s) for approximately 5 to 8 minutes to thaw.
5. Remove vials from the water bath prior to the last visible crystal of ice melting.
  Note: Do not exceed 15 minutes for each set of four vials.
6. Inspect vial(s) while still in the bag(s) to identify there is no leakage of vial contents.
7. Remove the RYONCIL vial(s) from the sealed plastic bag(s).
8. Inspect for foreign particulate matter (FPM). If FPM is found via visual inspection – DO NOT USE! Retain the offending vial(s). Call the Mesoblast contact number 844-889-MESO (6376).
9. Remove the tab from the RYONCIL vial cap to expose the vial stopper and wipe the exposed surface of the stopper with one provided sterile alcohol wipe.
10. Promptly withdraw the required amount of RYONCIL (based on actual patient body weight) from the vial(s). One syringe and an 18-gauge needle per thawed vial is required.
11. Carefully remove the needle from the syringe containing RYONCIL.
12. Attach the threaded lock cannula to the syringe.
13. Retrieve the infusion bag.
14. Wipe the membrane of the infusion bag interlink spike injection site with sterile alcohol wipe.
15. Insert 1 interlink blood bag spike into the outermost port on the infusion bag (leave the middle port for the infusion line.)
16. Attach the syringe to the spike and transfer the RYONCIL into the infusion bag.
17. Remove the syringe with the threaded lock cannula and discard the syringe and the threaded lock cannula.
18. Repeat for each syringe until the required volume of RYONCIL is added to the infusion bag.

Transfer of Plasma-Lyte® A into Infusion Bag

1. Retrieve the bag and 60 mL syringe containing Plasma-Lyte® A.
2. Verify the syringe contains 40mL of Plasma-Lyte® A.
3. Aseptically remove the 60 mL syringe with the threaded lock cannula containing the 40mL Plasma-Lyte® from the bag of Plasma-Lyte® A.
4. Use alcohol wipes to clean the membrane of the infusion bag interlink spike injection site.
5. Aseptically attach the 60mL syringe containing the Plasma-Lyte® A to the spike.
6. Slowly transfer the 40mL Plasma-Lyte® A into the infusion bag.
7. Gently mix cells with the Plasma-Lyte® A.
8. Remove the syringe with the threaded lock cannula and discard the syringe and threaded lock cannula.
9. Label the bag according to Institutional Policy.
10. Transport infusion bag to patient infusion area.

Administration

Note: Patient infusion must occur within 5 hours from the start time of first vial(s) of RYONCIL thaw.

- Administer RYONCIL under the supervision of a qualified health professional experienced in the management of SR-aGvHD.
- Administer RYONCIL using an infusion pump.
- Use blood filter with a pore size of 40-260 microns for infusion of RYONCIL.
- Flush lines per institutional practice and/or policy for cellular infusions.
- Pretreatment
  Premedicate patients with corticosteroids and antihistamines 30-60 minutes prior to administration of RYONCIL to reduce the potential for infusion reactions.
- Infusion Rates
  - For patients weighing 35 kg or more, infuse RYONCIL at a rate of no more than 6mL/ minute.
  - For patients weighing less than 35 kg, infuse RYONCIL over the course of 60 minutes.
- Discard unused, thawed RYONCIL vials per institutional policy.

3 DOSAGE FORMS AND STRENGTHS

RYONCIL is available as a cell suspension for intravenous infusion in a target concentration of 6.68 X 10^6 MSCs per mL in 3.8 mL at cryopreservation contained in a 6 mL cryovial.

Each 6 mL cryovial contains approximately 25 x 10^6 MSCs.

Cryopreserved MSCs are combined with Plasma-Lyte® A for administration.

4 CONTRAINDICATIONS

Do not use RYONCIL in patients with known hypersensitivity to dimethyl sulfoxide (DMSO) or porcine and bovine proteins.

5 WARNINGS AND PRECAUTIONS

5.1 Hypersensitivity and Acute Infusion Reactions

Hypersensitivity reactions including acute infusion reactions have occurred with RYONCIL administration [see Adverse Reactions (6.1)]. Serious hypersensitivity reactions, including anaphylaxis, may occur due to DMSO and trace amounts of porcine or bovine proteins. Signs and symptoms may include fever, dyspnea, and hypotension during or after RYONCIL infusion.

Premedicate patients with antihistamine and corticosteroids and monitor closely for signs and symptoms of hypersensitivity or acute infusion reactions.

If a hypersensitivity or infusion reaction occurs, interrupt RYONCIL infusion. Do not administer RYONCIL in patients who experience serious or life-threatening reactions.

5.2 Transmission of Infectious Agents

Transmission of infectious disease or agents may occur with RYONCIL administration because it contains cells from human donors and is manufactured using human, porcine and bovine-derived reagents. Donors are screened and tested for Human Immune-deficiency Virus 1 (HIV-1); Human Immune-deficiency Virus 2 (HIV-2); Hepatitis B Virus (HBV); Hepatitis C Virus (HCV); Human T-cell Leukemia-lymphoma Virus 1 (HTLV-1); Human T-cell Leukemia-lymphoma Virus 2 (HTLV-2); West Nile Virus (WNV); Cytomegalovirus (CMV); Epstein-Barr Virus (EBV); and Syphilis (Treponema pallidum). Only screening was performed for Creutzfeldt-Jakob disease (CJD) and communicable disease risks associated with xenotransplantation. RYONCIL cell banks are tested for human and animal viruses, retroviruses, bacteria, fungi, yeast, and mycoplasma. Human and animal-derived reagents are tested for human and animal viruses, bacteria, fungi, and mycoplasma before use. These measures do not eliminate the risk of transmitting these or other infectious diseases or agents.

5.3 Ectopic Tissue Formation

Ectopic tissue formation may occur following treatment with RYONCIL due to the ability of human mesenchymal stromal cells to differentiate into mesenchymal lineage cells such as bone, cartilage and fat cells.

6 ADVERSE REACTIONS

6.1 Clinical Trials Experience

Because clinical studies are conducted under widely varying conditions, adverse reaction rates observed in the clinical studies of a drug cannot be directly compared to rates in the clinical studies of another drug and may not reflect the rates observed in practice.

The safety data described in this section reflect exposure to RYONCIL in 54 patients in Study MSB-GVHD001 for the treatment of SR-aGvHD. Patients received intravenous infusion of RYONCIL at a dosage of 2 x 10^6 MSCs/kg twice a week for four consecutive weeks, for a total of eight infusions. Patients with partial or mixed response at Day 28 received additional infusions of RYONCIL 2 x 10^6 MSCs/kg once a week for an additional four weeks [see Clinical Studies (14)]. The median number of doses administered were 10 (range 1 to 16), and the treatment was administered over a median of 43 days (range 1 to 104 days).

Serious adverse reactions occurred in 35 patients (65%) including pyrexia (n=5;9%), respiratory failure (n=5;9%), pneumatosis intestinalis (n=4;7%) and staphylococcal bacteremia (n=2;<5%). Eight patients had discontinuation of RYONCIL treatment due to the following: acute infusion reactions (n=3), hypotension (n=1), gastroenteritis (n=1), and death (n=3).

Table 2 summarizes most common adverse reactions that occurred in ≥10% patients in Study MSB-GVHD001.

Table 2: Adverse Reactions** Occurring in ≥10% of Patients in Study MSB-GVHD001 (N=54)
Adverse Reactions | All Gradesa n (%) | Grade 3b n (%)
Viral infectious disorders* | 30 (56) | 8 (15)
Bacterial infectious disorders* | 24 (44) | 10 (19)
Infections - pathogen unspecified* | 22 (41) | 8 (15)
Pyrexia | 19 (35) | 2 (4)
Hemorrhage* | 15 (28) | 4 (7)
Edema* | 12 (22) | 1 (2)
Abdominal pain | 11 (20) | 4 (7)
Hypertension | 11 (20) | 3 (6)
Vomiting | 10 (19) | 3 (6)
Arrhythmia* | 9 (17) | 2 (4)
Diarrhea | 9 (17) | 1 (2)
Rash* | 9 (17) | 0 (0)
Arthralgia | 8 (15) | 0 (0)
Fungal infectious disorders* | 8 (15) | 2 (4)
Hypotension | 8 (15) | 2 (4)
Cough | 7 (13) | 0 (0)
Respiratory Failure | 6 (11) | 6 (11)
a Based on National Cancer Institute Adverse Event Common Toxicity Criteria version 4.03
b No grade 4 or 5 adverse reactions occurred in the study
*Is a composite that includes multiple related terms
**Includes adverse reactions up to 100 days following RYONCIL treatment

Table 3 presents the most common grade 3 or 4 laboratory abnormalities that worsened from baseline in ≥10% of patients

Table 3: Grade 3 or 4 Laboratory Abnormalities that Worsened from Baseline in ≥ 10% of Patients in Study MSB-GVHD001 (N=54)
Laboratory Parameter | Grade 3 or highera %
Gamma-glutamyl transferase increased | 32
Thrombocytopenia | 28
Blood bilirubin increased | 11
a Based on National Cancer Institute Adverse Event Common Toxicity Criteria version 4.03

8 USE IN SPECIFIC POPULATIONS

8.1 Pregnancy

Risk Summary

There are no available data for RYONCIL use in pregnant women. No animal reproductive and developmental toxicity studies have been conducted with RYONCIL to assess whether it can cause fetal harm when administered to a pregnant woman. It is not known if RYONCIL has the potential to be transferred to the fetus. Therefore, RYONCIL is not recommended for women who are pregnant. In the U.S. general population, the estimated background risk of major birth defects and miscarriage in clinically recognized pregnancies is 2-4% and 10-20%, respectively.

8.2 Lactation

Risk Summary

There is no information regarding the presence of RYONCIL in human milk, the effect on the breastfed infant, and the effects on milk production. The developmental and health benefits of breastfeeding should be considered along with the mother’s clinical need for RYONCIL and any potential adverse effects on the breastfed infant from RYONCIL or from the underlying maternal condition.

8.4 Pediatric Use

The safety and effectiveness of RYONCIL for treatment of SR-GvHD have been established in pediatric patients 2 months of age and older. The use of RYONCIL in these age groups is supported by evidence from an adequate and well-controlled trial [see Adverse Reactions (6) and Clinical Studies (14)].

11 DESCRIPTION

RYONCIL is provided as a frozen cell suspension in a cryogenic vial. The active ingredient in RYONCIL is comprised of culture-expanded mesenchymal stromal cells (MSCs) isolated from the bone marrow of healthy human adult donors. Each cryovial contains nominally 25 x 10^6 MSCs in 3.8 mL (a target concentration 6.68 x 10^6 cells/mL) formulated in Plasma Lyte®-A (70% v/v), Human Serum Albumin (HSA) Solution (25%) (20% v/v) and Dimethyl sulfoxide (DMSO) (10% v/v). The product is thawed and combined with Plasma-Lyte® A prior to intravenous administration.

12 CLINICAL PHARMACOLOGY

12.1 Mechanism of Action

The mechanism of action for RYONCIL is not clear but may be related to immunomodulatory effects. Data from in vitro studies demonstrate that MSCs inhibit T cell activation as measured by proliferation and secretion of pro-inflammatory cytokines. Acute GvHD occurs when alloreactive donor-derived T cells within the donated tissue (graft) trigger an immunological response, and alloreactive donor-derived T cells play a role in mediating the systemic inflammation, cytotoxicity and potential end organ damage associated with aGvHD.

12.2 Pharmacodynamics

Human pharmacodynamic data were obtained from analysis of blood samples in pediatric subjects with SR-aGvHD (n=40; age range 0.6-17 years) following treatment with RYONCIL at a dose of 2x10^6 cells/kg. At Baseline, elevated levels of tumor necrosis factor receptor type I (TNFR1) and suppressor of tumorigenicity 2 (ST2) were observed consistent with the inflammatory state of aGvHD. Treatment with RYONCIL reduced the levels of TNFR1 and ST2 by 79% and 75%, respectively, at Day 180 as compared to baseline values. Further, the circulating levels of CD3+CD4+CD25+HLA-DR+ T cells, which represent activated T cells, were reduced by 64% at Day 180 following treatment with RYONCIL as compared to the baseline values.

12.3 Pharmacokinetics

No studies have been performed to evaluate the pharmacokinetics of RYONCIL.

13 NONCLINICAL TOXICOLOGY

13.1 Carcinogenesis, Mutagenesis, Impairment of Fertility

No animal studies have been performed to evaluate the effects of RYONCIL on carcinogenesis, mutagenesis or impairment of fertility.

14 CLINICAL STUDIES

The efficacy of RYONCIL was evaluated in a multicenter, prospective, single-arm study (MSB-GVHD 001; NCT02336230). The study enrolled pediatric patients with SR-GvHD Grade B to D (excluding Grade B skin alone) as per International Blood and Marrow Transplantation Registry Severity Index Criteria (IBMTR) after receiving allogeneic hematopoietic stem cell transplantation (HSCT). SR-aGvHD was defined as aGvHD that progressed within 3 days or did not improve within 7 consecutive days of treatment with methylprednisolone 2 mg/kg/day or equivalent. Patients who received a second line therapy for aGvHD prior to screening were excluded.

RYONCIL was administered by intravenous infusion at a dosage of 2 x 10^6 MSCs/kg twice a week for four consecutive weeks, for a total of eight infusions. Patients with partial or mixed response at Day 28 received additional infusions of RYONCIL 2 x 10^6 MSCs/kg once a week for an additional four consecutive weeks. Patients with complete response at Day 28 who experienced recurrence of aGvHD received infusions of RYONCIL 2 x 10^6 MSCs/kg twice a week for an additional four consecutive weeks.

A total of 55 patients were enrolled, and 54 were treated with RYONCIL. Among the treated patients (n=54), the demographic characteristics were as follows: median age was 7 years (range: 7 months to 17 years); 36% were females; 56% were White, 19% reported “other” race, 15% were Black, 6% were Asian, 6% American Indian or Alaska Native, 33% were Hispanic and 65% were non-Hispanic. Among enrolled patients, hematologic malignancies (67%) and non-malignant diseases (33%) were the underlying reasons for allogenic HSCT. SR-GvHD severity was as follows at baseline: Grade B (11%), Grade C (43%), Grade D (46%). Organ involvement at baseline were as follows: skin alone (26%), lower gastrointestinal tract only (39%), multi-organ involvement (35%). The median duration of prior corticosteroid treatment at baseline was 8 days (range: 2 to 46 days).

The main efficacy outcome measures were Day-28 overall response rate (complete response rate and partial response rate) and the duration of response.

The efficacy results are summarized in Table 4.

Table 4: Efficacy Results for Study MSB-GVHD001
Response at Day 28 | N=54
Overall Response Rate n (%) 95% CIa | 38 (70%) 56.4, 82.0
Durationb (days) Median (range) | 54 (7, 159+)
Complete Response Ratec n (%) 95% CIa | 16 (30%) 18.0, 43.6
Partial Response Rated n (%) 95% CIa | 22 (41%) 27.6, 55.0
CI=confidence interval
a Two-sided exact binomial confidence interval at the 95% level
b Duration of response was calculated from Day-28 response to either progression (worsening by one stage in any organ without improvement in other organs in comparison to prior response assessment), new systemic therapy for aGvHD or death from any cause.
c Complete response was defined as resolution of aGvHD in all involved organs as per IBMTR grading system.
d Partial response was defined as organ improvement of at least one stage without worsening of any other organ as per IBMTR grading system.

Overall response rate at Day 28 by baseline disease severity is as follows: Grade B (3/6; 50%), Grade C (16/23; 70%), and Grade D (19/25; 76%).

Among the 38 responders, the median time from Day-28 response to either death or need for systemic therapy for aGvHD (non-RYONCIL systemic therapy for aGvHD or increase in the dose of corticosteroids to methylprednisolone 2 mg/kg or equivalent) was 111.5 days (range 9, 182+).

16 HOW SUPPLIED/STORAGE AND HANDLING

RYONCIL is supplied as a sterile, cryopreserved cell suspension of ex-vivo culture-expanded allogeneic bone marrow-derived mesenchymal stromal cells (MSC) in vials.

RYONCIL is provided as a customized kit to meet dosing requirements for a single dose for each patient [see Dosage and Administration (2.1)], with each kit containing:

- Cartons containing sufficient RYONCIL for one infusion based on the patient weight (see Table 5)
- Sufficient alcohol wipes for preparation of the RYONCIL infusions.

Kit sizes and National Drug Codes (NDC) are provided in Table 5.

Table 5: RYONCIL Kit Sizes
Patient weight (kg) | Kit contents (single infusion) |  |  |  |  | Number of kits needed for:
Patient weight (kg) | 4-vial cartons | 1-vial cartons | Total cartons | Number of alcohol wipes | NDC Number | Initial course | 2nd course | Relapse after CR
<12.5 | 0 | 1 | 1 | 1 | 73648-111-01 | 8 | 4 | 8
12.5-<25 | 0 | 2 | 2 | 2 | 73648-112-02 | 8 | 4 | 8
25-<37.5 | 0 | 3 | 3 | 3 | 73648-113-03 | 8 | 4 | 8
37.5-<50 | 1 | 0 | 1 | 4 | 73648-114-01 | 8 | 4 | 8
50-<62.5 | 1 | 1 | 2 | 5 | 73648-115-02 | 8 | 4 | 8
62.5-<75 | 1 | 2 | 3 | 6 | 73648-116-03 | 8 | 4 | 8
75-<87.5 | 1 | 3 | 4 | 7 | 73648-117-04 | 8 | 4 | 8
87.5-<100 | 2 | 0 | 2 | 8 | 73648-118-02 | 8 | 4 | 8
100-<112.5 | 2 | 1 | 3 | 9 | 73648-119-03 | 8 | 4 | 8
112.5-<125 | 2 | 2 | 4 | 10 | 73648-120-04 | 8 | 4 | 8
125-<137.5 | 2 | 3 | 5 | 11 | 73648-121-05 | 8 | 4 | 8
137.5-<150 | 3 | 0 | 3 | 12 | 73648-122-03 | 8 | 4 | 8

RYONCIL is shipped to the clinical facility in a liquid nitrogen dry shipper maintained at a temperature of ≤ -135°C.

Storage conditions: RYONCIL must remain frozen at ≤ -135°C in liquid nitrogen vapor phase until thawed immediately prior to administration.

Handling: Restrict preparation and administration of RYONCIL to a medical facility in which the medical personnel are trained in aseptic technique.

Disposal: Dispose empty or partially used RYONCIL vials according to the institutional guidelines for disposal of biohazard materials.

Do not save thawed RYONCIL vials for future use.

17 PATIENT COUNSELING INFORMATION

Discuss the following with patients and/or caregivers.

- Hypersensitivity and Acute infusion reactions: Inform patients and/or caregivers that hypersensitivity and acute infusion reactions due to the presence of porcine and bovine protein, and DMSO may occur with RYONCIL infusion. Advise patients and/or caregivers to seek immediate medical evaluation if any signs and symptoms of hypersensitivity or acute infusion reactions occur, such as fever, rash or hives, low blood pressure, breathing problems [see Warnings and Precautions (5.1].
- Transmission of Infectious Agents: Inform patients and/or caregivers about the possible risk of transmission of infectious agents with RYONCIL administration [see Warnings and Precautions (5.2)].
- Ectopic Tissue Formation: Inform patients and/or caregivers about the possible risk of ectopic tissue formation with RYONCIL administration [see Warnings and Precautions (5.3)].

Manufactured for:
Mesoblast, Inc.
1114 Sixth Avenue, Fourth Floor
New York, NY 10036
US License number: 2140

RYONCIL is a registered trademark of Mesoblast. All rights reserved.
©2024 Mesoblast, Inc. All rights Reserved
V 3

PACKAGE/LABEL PRINCIPAL DISPLAY PANEL

remestemcel-L-rknd

Ryoncil®

Target 25 X 10^6/ 3.8mL
(6.68 x 10^6/mL)

For intravenous administration after thaw
and resuspension
See Prescribing Information for directions for use.
Store at ≤ -135°C
Single–use vial
Discard unused portion

Manufactured for Mesoblast Inc.

Rx only

PACKAGE/LABEL PRINCIPAL DISPLAY PANEL

NDC 73648-154-01

remestemcel-L-rknd

Ryoncil®

Suspension for IV Infusion

Allogeneic bone marrow-derived mesenchymal stromal cells
Target 25 X 10^6/ 3.8mL (6.68 x 10^6/mL)
Single–use vial. Discard unused portion.

For intravenous administration after thaw and resuspension

Rx only
Sterile. No preservative.

PACKAGE/LABEL PRINCIPAL DISPLAY PANEL

NDC 73648-154-04

remestemcel-L-rknd

Ryoncil®

Suspension for IV Infusion

Allogeneic bone marrow-derived mesenchymal stromal cells
Target 25 X 10^6/ 3.8mL (6.68 x 10^6/mL)
Single–use vial. Discard unused portion.

For intravenous administration after thaw and resuspension

Rx only
Sterile. No preservative.

PACKAGE/LABEL PRINCIPAL DISPLAY PANEL

NDC 73648-111-01
remestemcel-L-rknd
Ryoncil®

Suspension for IV Infusion
Allogeneic bone marrow-derived mesenchymal stromal cells
Target 25 X 10^6/ 3.8mL (6.68 x 10^6/mL)

Kit for Patient Weight:
<12.5 kg

Kit Contents:
1 X single vial carton
1 Alcohol Wipe

Single–use vial. Discard unused portion.
For intravenous administration after thaw and resuspension
Rx only
Sterile. No preservative.
See Prescribing Information for directions for use.
Complete infusion within 5 HOURS of thawing and resuspension
of RYONCIL®.
Each vial contains a target of 25 x 10^6 cells / 3.8 mL.
Cryopreserved in: Human Serum Albumin Solution 20% v/v
(containing 5% w/v Human Serum Albumin), Plasma Lyte-A 70 %
v/v, dimethyl sulfoxide (DMSO) 10% v/v.
Contains known sensitizing substances DMSO or Porcine and
Bovine proteins (see Prescribing Information, WARNINGS AND
PRECAUTIONS).
Store at ≤- 135°C; vapor phase of liquid nitrogen
No U.S. standard of potency.

Manufactured for Mesoblast Inc.
1114 Sixth Avenue, Fourth Floor
New York, NY 10036
U.S. License number: 2140

GTIN: XXXXXXXXXXXXXX
SN: XXXXXXXXXXXX
LOT: XXXXXXX
EXP: MMMYYYY

PNTC-1154.024

PACKAGE/LABEL PRINCIPAL DISPLAY PANEL

NDC 73648-112-02
remestemcel-L-rknd
Ryoncil®

Suspension for IV Infusion
Allogeneic bone marrow-derived mesenchymal stromal cells
Target 25 X 10^6/ 3.8mL (6.68 x 10^6/mL)

Kit for Patient Weight:
12.5 kg – <25 kg

Kit Contents:
2 X single vial cartons
2 Alcohol Wipes

Single–use vial. Discard unused portion.
For intravenous administration after thaw and resuspension
Rx only
Sterile. No preservative.
See Prescribing Information for directions for use.
Complete infusion within 5 HOURS of thawing and resuspension
of RYONCIL®.
Each vial contains a target of 25 x 10^6 cells / 3.8 mL.
Cryopreserved in: Human Serum Albumin Solution 20% v/v
(containing 5% w/v Human Serum Albumin), Plasma Lyte-A 70 %
v/v, dimethyl sulfoxide (DMSO) 10% v/v.
Contains known sensitizing substances DMSO or Porcine and
Bovine proteins (see Prescribing Information, WARNINGS AND
PRECAUTIONS).
Store at ≤- 135°C; vapor phase of liquid nitrogen
No U.S. standard of potency.

Manufactured for Mesoblast Inc.
1114 Sixth Avenue, Fourth Floor
New York, NY 10036
U.S. License number: 2140

GTIN: XXXXXXXXXXXXXX
SN: XXXXXXXXXXXX
LOT: XXXXXXX
EXP: MMMYYYY

PNTC-1154.025

PACKAGE/LABEL PRINCIPAL DISPLAY PANEL

NDC 73648-113-03
remestemcel-L-rknd
Ryoncil®

Suspension for IV Infusion
Allogeneic bone marrow-derived mesenchymal stromal cells
Target 25 X 10^6/ 3.8mL (6.68 x 10^6/mL)

Kit for Patient Weight:
25 kg – <37.5 kg

Kit Contents:
3 X single vial cartons
3 Alcohol Wipes

Single–use vial. Discard unused portion.
For intravenous administration after thaw and resuspension
Rx only
Sterile. No preservative.
See Prescribing Information for directions for use.
Complete infusion within 5 HOURS of thawing and resuspension
of RYONCIL®.
Each vial contains a target of 25 x 10^6 cells / 3.8 mL.
Cryopreserved in: Human Serum Albumin Solution 20% v/v
(containing 5% w/v Human Serum Albumin), Plasma Lyte-A 70 %
v/v, dimethyl sulfoxide (DMSO) 10% v/v.
Contains known sensitizing substances DMSO or Porcine and
Bovine proteins (see Prescribing Information, WARNINGS AND
PRECAUTIONS).
Store at ≤- 135°C; vapor phase of liquid nitrogen
No U.S. standard of potency.

Manufactured for Mesoblast Inc.
1114 Sixth Avenue, Fourth Floor
New York, NY 10036
U.S. License number: 2140

GTIN: XXXXXXXXXXXXXX
SN: XXXXXXXXXXXX
LOT: XXXXXXX
EXP: MMMYYYY

PNTC-1154.026

PACKAGE/LABEL PRINCIPAL DISPLAY PANEL

NDC 73648-114-01
remestemcel-L-rknd
Ryoncil®

Suspension for IV Infusion
Allogeneic bone marrow-derived mesenchymal stromal cells
Target 25 X 10^6/ 3.8mL (6.68 x 10^6/mL)

Kit for Patient Weight:
37.5 kg – <50 kg

Kit Contents:
1 X 4-vial carton
4 Alcohol Wipes

Single–use vial. Discard unused portion.
For intravenous administration after thaw and resuspension
Rx only
Sterile. No preservative.
See Prescribing Information for directions for use.
Complete infusion within 5 HOURS of thawing and resuspension
of RYONCIL®.
Each vial contains a target of 25 x 10^6 cells / 3.8 mL.
Cryopreserved in: Human Serum Albumin Solution 20% v/v
(containing 5% w/v Human Serum Albumin), Plasma Lyte-A 70 %
v/v, dimethyl sulfoxide (DMSO) 10% v/v.
Contains known sensitizing substances DMSO or Porcine and
Bovine proteins (see Prescribing Information, WARNINGS AND
PRECAUTIONS).
Store at ≤- 135°C; vapor phase of liquid nitrogen
No U.S. standard of potency.

Manufactured for Mesoblast Inc.
1114 Sixth Avenue, Fourth Floor
New York, NY 10036
U.S. License number: 2140

GTIN: XXXXXXXXXXXXXX
SN: XXXXXXXXXXXX
LOT: XXXXXXX
EXP: MMMYYYY

PNTC-1154.027

PACKAGE/LABEL PRINCIPAL DISPLAY PANEL

NDC 73648-115-02
remestemcel-L-rknd
Ryoncil®

Suspension for IV Infusion
Allogeneic bone marrow-derived mesenchymal stromal cells
Target 25 X 10^6/ 3.8mL (6.68 x 10^6/mL)

Kit for Patient Weight:
50 kg – <62.5 kg

Kit Contents:
1 X single vial carton
1 X 4-vial carton
5 Alcohol Wipes

Single–use vial. Discard unused portion.
For intravenous administration after thaw and resuspension
Rx only
Sterile. No preservative.
See Prescribing Information for directions for use.
Complete infusion within 5 HOURS of thawing and resuspension
of RYONCIL®.
Each vial contains a target of 25 x 10^6 cells / 3.8 mL.
Cryopreserved in: Human Serum Albumin Solution 20% v/v
(containing 5% w/v Human Serum Albumin), Plasma Lyte-A 70 %
v/v, dimethyl sulfoxide (DMSO) 10% v/v.
Contains known sensitizing substances DMSO or Porcine and
Bovine proteins (see Prescribing Information, WARNINGS AND
PRECAUTIONS).
Store at ≤- 135°C; vapor phase of liquid nitrogen
No U.S. standard of potency.

Manufactured for Mesoblast Inc.
1114 Sixth Avenue, Fourth Floor
New York, NY 10036
U.S. License number: 2140

GTIN: XXXXXXXXXXXXXX
SN: XXXXXXXXXXXX
LOT: XXXXXXX
EXP: MMMYYYY

PNTC-1154.028

PACKAGE/LABEL PRINCIPAL DISPLAY PANEL

NDC 73648-116-03
remestemcel-L-rknd
Ryoncil®

Suspension for IV Infusion
Allogeneic bone marrow-derived mesenchymal stromal cells
Target 25 X 10^6/ 3.8mL (6.68 x 10^6/mL)

Kit for Patient Weight:
62.5 kg – <75 kg

Kit Contents:
2 X single vial cartons
1 X 4-vial carton
6 Alcohol Wipes

Single–use vial. Discard unused portion.
For intravenous administration after thaw and resuspension
Rx only
Sterile. No preservative.
See Prescribing Information for directions for use.
Complete infusion within 5 HOURS of thawing and resuspension
of RYONCIL®.
Each vial contains a target of 25 x 10^6 cells / 3.8 mL.
Cryopreserved in: Human Serum Albumin Solution 20% v/v
(containing 5% w/v Human Serum Albumin), Plasma Lyte-A 70 %
v/v, dimethyl sulfoxide (DMSO) 10% v/v.
Contains known sensitizing substances DMSO or Porcine and
Bovine proteins (see Prescribing Information, WARNINGS AND
PRECAUTIONS).
Store at ≤- 135°C; vapor phase of liquid nitrogen
No U.S. standard of potency.

Manufactured for Mesoblast Inc.
1114 Sixth Avenue, Fourth Floor
New York, NY 10036
U.S. License number: 2140

GTIN: XXXXXXXXXXXXXX
SN: XXXXXXXXXXXX
LOT: XXXXXXX
EXP: MMMYYYY

PNTC-1154.029

PACKAGE/LABEL PRINCIPAL DISPLAY PANEL

NDC 73648-117-04
remestemcel-L-rknd
Ryoncil®

Suspension for IV Infusion
Allogeneic bone marrow-derived mesenchymal stromal cells
Target 25 X 10^6/ 3.8mL (6.68 x 10^6/mL)

Kit for Patient Weight:
75 kg – <87.5 kg

Kit Contents:
3 X single vial cartons
1 X 4-vial carton
7 Alcohol Wipes

Single–use vial. Discard unused portion.
For intravenous administration after thaw and resuspension
Rx only
Sterile. No preservative.
See Prescribing Information for directions for use.
Complete infusion within 5 HOURS of thawing and resuspension
of RYONCIL®.
Each vial contains a target of 25 x 10^6 cells / 3.8 mL.
Cryopreserved in: Human Serum Albumin Solution 20% v/v
(containing 5% w/v Human Serum Albumin), Plasma Lyte-A 70 %
v/v, dimethyl sulfoxide (DMSO) 10% v/v.
Contains known sensitizing substances DMSO or Porcine and
Bovine proteins (see Prescribing Information, WARNINGS AND
PRECAUTIONS).
Store at ≤- 135°C; vapor phase of liquid nitrogen
No U.S. standard of potency.

Manufactured for Mesoblast Inc.
1114 Sixth Avenue, Fourth Floor
New York, NY 10036
U.S. License number: 2140

GTIN: XXXXXXXXXXXXXX
SN: XXXXXXXXXXXX
LOT: XXXXXXX
EXP: MMMYYYY

PNTC-1154.030

PACKAGE/LABEL PRINCIPAL DISPLAY PANEL

NDC 73648-118-02
remestemcel-L-rknd
Ryoncil®

Suspension for IV Infusion
Allogeneic bone marrow-derived mesenchymal stromal cells
Target 25 X 10^6/ 3.8mL (6.68 x 10^6/mL)

Kit for Patient Weight:
87.5 kg – <100 kg

Kit Contents:
2 X 4-vial cartons
8 Alcohol Wipes

Single–use vial. Discard unused portion.
For intravenous administration after thaw and resuspension
Rx only
Sterile. No preservative.
See Prescribing Information for directions for use.
Complete infusion within 5 HOURS of thawing and resuspension
of RYONCIL®.
Each vial contains a target of 25 x 10^6 cells / 3.8 mL.
Cryopreserved in: Human Serum Albumin Solution 20% v/v
(containing 5% w/v Human Serum Albumin), Plasma Lyte-A 70 %
v/v, dimethyl sulfoxide (DMSO) 10% v/v.
Contains known sensitizing substances DMSO or Porcine and
Bovine proteins (see Prescribing Information, WARNINGS AND
PRECAUTIONS).
Store at ≤- 135°C; vapor phase of liquid nitrogen
No U.S. standard of potency.

Manufactured for Mesoblast Inc.
1114 Sixth Avenue, Fourth Floor
New York, NY 10036
U.S. License number: 2140

GTIN: XXXXXXXXXXXXXX
SN: XXXXXXXXXXXX
LOT: XXXXXXX
EXP: MMMYYYY

PNTC-1154.031

PACKAGE/LABEL PRINCIPAL DISPLAY PANEL

NDC 73648-119-03
remestemcel-L-rknd
Ryoncil®

Suspension for IV Infusion
Allogeneic bone marrow-derived mesenchymal stromal cells
Target 25 X 10^6/ 3.8mL (6.68 x 10^6/mL)

Kit for Patient Weight:
100 - < 112.5 kg

Kit Contents:
1 x Single vial carton
2 x 4-vial cartons
9 Alcohol wipes

Single–use vial. Discard unused portion.
For intravenous administration after thaw and resuspension
Rx only
Sterile. No preservative.
See Prescribing Information for directions for use.
Complete infusion within 5 HOURS of thawing and resuspension
of RYONCIL®.
Each vial contains a target of 25 x 10^6 cells / 3.8 mL.
Cryopreserved in: Human Serum Albumin Solution 20% v/v
(containing 5% w/v Human Serum Albumin), Plasma Lyte-A 70 %
v/v, dimethyl sulfoxide (DMSO) 10% v/v.
Contains known sensitizing substances DMSO or Porcine and
Bovine proteins (see Prescribing Information, WARNINGS AND
PRECAUTIONS).
Store at ≤- 135°C; vapor phase of liquid nitrogen
No U.S. standard of potency.

Manufactured for Mesoblast Inc.
1114 Sixth Avenue, Fourth Floor
New York, NY 10036
U.S. License number: 2140

GTIN: XXXXXXXXXXXXXX
SN: XXXXXXXXXXXX
LOT: XXXXXXX
EXP: MMMYYYY

PNTC-1154.038

PACKAGE/LABEL PRINCIPAL DISPLAY PANEL

NDC 73648-120-04
remestemcel-L-rknd
Ryoncil®

Suspension for IV Infusion
Allogeneic bone marrow-derived mesenchymal stromal cells
Target 25 X 10^6/ 3.8mL (6.68 x 10^6/mL)

Kit for Patient Weight:
112.5 - < 125 kg

Kit Contents:
2 x Single vial carton
2 x 4-vial cartons
10 Alcohol wipes

Single–use vial. Discard unused portion.
For intravenous administration after thaw and resuspension
Rx only
Sterile. No preservative.
See Prescribing Information for directions for use.
Complete infusion within 5 HOURS of thawing and resuspension
of RYONCIL®.
Each vial contains a target of 25 x 10^6 cells / 3.8 mL.
Cryopreserved in: Human Serum Albumin Solution 20% v/v
(containing 5% w/v Human Serum Albumin), Plasma Lyte-A 70 %
v/v, dimethyl sulfoxide (DMSO) 10% v/v.
Contains known sensitizing substances DMSO or Porcine and
Bovine proteins (see Prescribing Information, WARNINGS AND
PRECAUTIONS).
Store at ≤- 135°C; vapor phase of liquid nitrogen
No U.S. standard of potency.

Manufactured for Mesoblast Inc.
1114 Sixth Avenue, Fourth Floor
New York, NY 10036
U.S. License number: 2140

GTIN: XXXXXXXXXXXXXX
SN: XXXXXXXXXXXX
LOT: XXXXXXX
EXP: MMMYYYY

PNTC-1154.039

PACKAGE/LABEL PRINCIPAL DISPLAY PANEL

NDC 73648-121-05
remestemcel-L-rknd
Ryoncil®

Suspension for IV Infusion
Allogeneic bone marrow-derived mesenchymal stromal cells
Target 25 X 10^6/ 3.8mL (6.68 x 10^6/mL)

Kit for Patient Weight:
125 - < 137.5 kg

Kit Contents:
3 x Single vial carton
2 x 4-vial cartons
11 Alcohol wipes

Single–use vial. Discard unused portion.
For intravenous administration after thaw and resuspension
Rx only
Sterile. No preservative.
See Prescribing Information for directions for use.
Complete infusion within 5 HOURS of thawing and resuspension
of RYONCIL®.
Each vial contains a target of 25 x 10^6 cells / 3.8 mL.
Cryopreserved in: Human Serum Albumin Solution 20% v/v
(containing 5% w/v Human Serum Albumin), Plasma Lyte-A 70 %
v/v, dimethyl sulfoxide (DMSO) 10% v/v.
Contains known sensitizing substances DMSO or Porcine and
Bovine proteins (see Prescribing Information, WARNINGS AND
PRECAUTIONS).
Store at ≤- 135°C; vapor phase of liquid nitrogen
No U.S. standard of potency.

Manufactured for Mesoblast Inc.
1114 Sixth Avenue, Fourth Floor
New York, NY 10036
U.S. License number: 2140

GTIN: XXXXXXXXXXXXXX
SN: XXXXXXXXXXXX
LOT: XXXXXXX
EXP: MMMYYYY

PNTC-1154.040

PACKAGE/LABEL PRINCIPAL DISPLAY PANEL

NDC 73648-122-03
remestemcel-L-rknd
Ryoncil®

Suspension for IV Infusion
Allogeneic bone marrow-derived mesenchymal stromal cells
Target 25 X 10^6/ 3.8mL (6.68 x 10^6/mL)

Kit for Patient Weight:
137.5 - < 150 kg

Kit Contents:
3 x 4-vial cartons
12 Alcohol wipes

Single–use vial. Discard unused portion.
For intravenous administration after thaw and resuspension
Rx only
Sterile. No preservative.
See Prescribing Information for directions for use.
Complete infusion within 5 HOURS of thawing and resuspension
of RYONCIL®.
Each vial contains a target of 25 x 10^6 cells / 3.8 mL.
Cryopreserved in: Human Serum Albumin Solution 20% v/v
(containing 5% w/v Human Serum Albumin), Plasma Lyte-A 70 %
v/v, dimethyl sulfoxide (DMSO) 10% v/v.
Contains known sensitizing substances DMSO or Porcine and
Bovine proteins (see Prescribing Information, WARNINGS AND
PRECAUTIONS).
Store at ≤- 135°C; vapor phase of liquid nitrogen
No U.S. standard of potency.

Manufactured for Mesoblast Inc.
1114 Sixth Avenue, Fourth Floor
New York, NY 10036
U.S. License number: 2140

GTIN: XXXXXXXXXXXXXX
SN: XXXXXXXXXXXX
LOT: XXXXXXX
EXP: MMMYYYY

PNTC-1154.041